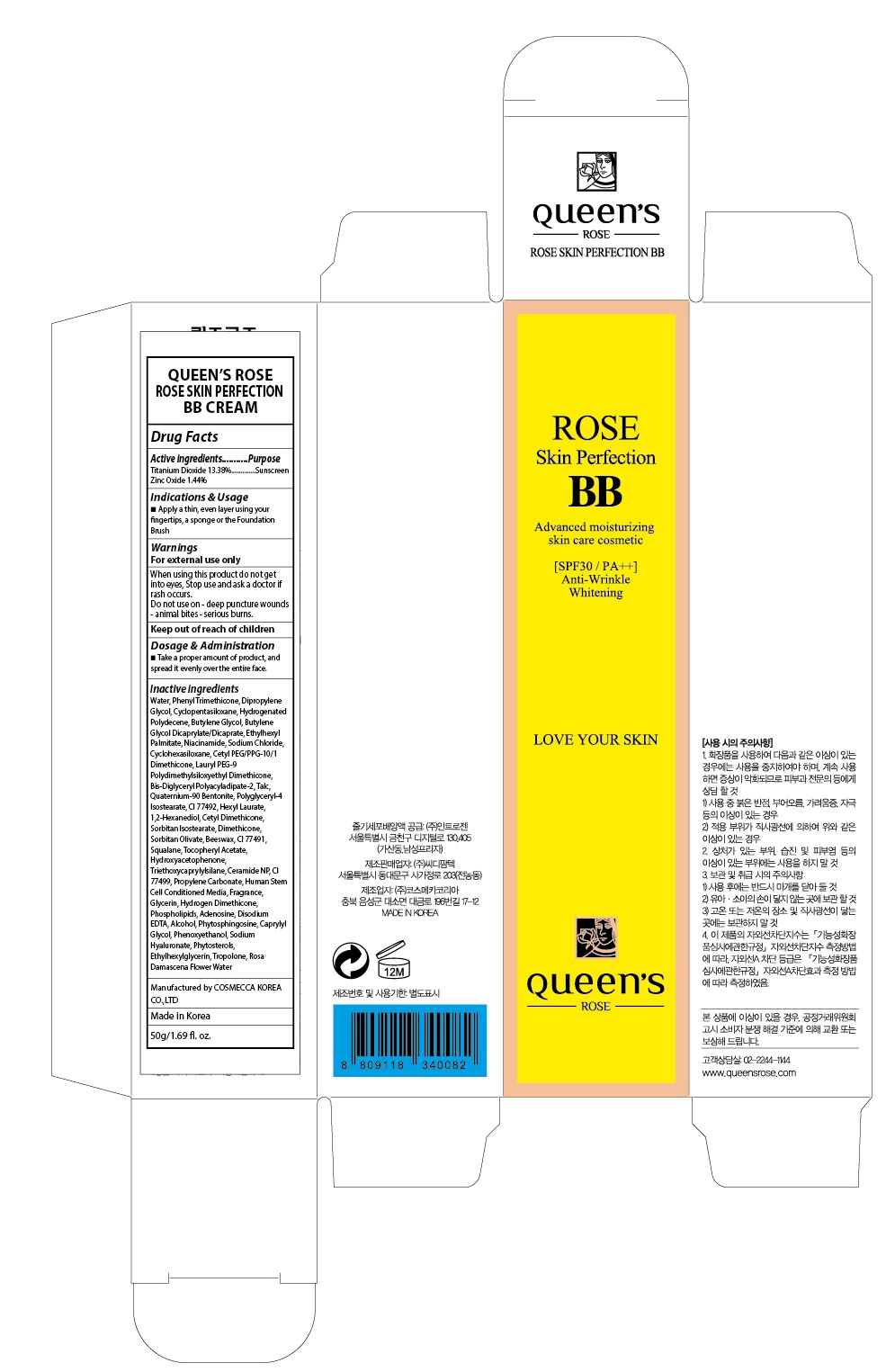 DRUG LABEL: QUEENS ROSE ROSE SKIN PERFECTION BB
NDC: 71252-110 | Form: CREAM
Manufacturer: Cdpharmtec Co.,ltd
Category: otc | Type: HUMAN OTC DRUG LABEL
Date: 20170324

ACTIVE INGREDIENTS: Titanium Dioxide 6.69 g/50 g; Zinc Oxide 0.72 g/50 g
INACTIVE INGREDIENTS: Water; Phenyl Trimethicone

ACTIVE INGREDIENT

Active ingredients: Titanium Dioxide 13.38%, Zinc Oxide 1.44%

INACTIVE INGREDIENT

Inactive ingredients: Water, Phenyl Trimethicone, Dipropylene Glycol, Cyclopentasiloxane, Hydrogenated Polydecene, Butylene Glycol, Butylene Glycol Dicaprylate/Dicaprate, Ethylhexyl Palmitate, Niacinamide, Sodium Chloride, Cyclohexasiloxane, Cetyl PEG/PPG-10/1 Dimethicone, Lauryl PEG-9 Polydimethylsiloxyethyl Dimethicone, Bis-Diglyceryl Polyacyladipate-2, Talc, Quaternium-90 Bentonite, Polyglyceryl-4 Isostearate, CI 77492, Hexyl Laurate, 1,2-Hexanediol, Cetyl Dimethicone, Sorbitan Isostearate, Dimethicone, Sorbitan Olivate, Beeswax, CI 77491, Squalane, Tocopheryl Acetate, Hydroxyacetophenone, Triethoxycaprylylsilane, Ceramide NP, CI 77499, Propylene Carbonate, Human Stem Cell Conditioned Media, Fragrance, Glycerin, Hydrogen Dimethicone, Phospholipids, Adenosine, Disodium EDTA, Alcohol, Phytosphingosine, Caprylyl Glycol, Phenoxyethanol, Sodium Hyaluronate, Phytosterols, Ethylhexylglycerin, Tropolone, Rosa Damascena Flower Water

PURPOSE

Purpose: Sunscreen

WARNINGS

Warnings: For external use only When using this product do not get into eyes, Stop use and ask a doctor if rash occurs. Do not use on - deep puncture wounds - animal bites - serious burns.

Keep out of reach of children

DESCRIPTION

Indications & Usage: Apply a thin, even layer using your fingertips, a sponge or the Foundation Brush

Dosage & Administration: Take a proper amount of the product and spread it evenly over the entire face